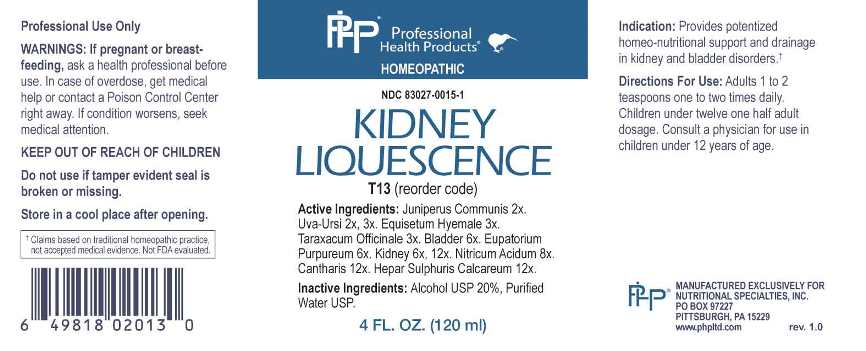 DRUG LABEL: Kidney Liquescence
NDC: 83027-0015 | Form: LIQUID
Manufacturer: Nutritional Specialties, Inc.
Category: homeopathic | Type: HUMAN OTC DRUG LABEL
Date: 20240911

ACTIVE INGREDIENTS: JUNIPER BERRY 2 [hp_X]/1 mL; ARCTOSTAPHYLOS UVA-URSI LEAF 2 [hp_X]/1 mL; EQUISETUM HYEMALE WHOLE 3 [hp_X]/1 mL; TARAXACUM OFFICINALE 3 [hp_X]/1 mL; SUS SCROFA URINARY BLADDER 6 [hp_X]/1 mL; EUTROCHIUM PURPUREUM ROOT 6 [hp_X]/1 mL; PORK KIDNEY 6 [hp_X]/1 mL; NITRIC ACID 8 [hp_X]/1 mL; LYTTA VESICATORIA 12 [hp_X]/1 mL; CALCIUM SULFIDE 12 [hp_X]/1 mL
INACTIVE INGREDIENTS: WATER; ALCOHOL

DRUG FACTS:

ACTIVE INGREDIENTS:

Juniperus Communis 2X, Uva-Ursi 2X, 3X, Equisetum Hyemale 3X, Taraxacum Officinale 3X, Urinary Bladder 6X, Eupatorium Purpureum 6X, Kidney 6X, 12X, Nitricum Acidum 8X, Cantharis 12X, Hepar Sulphuris Calcareum 12X.

PURPOSE:

Provides potentized homeo-nutritional support and drainage in kidney and bladder disorders.†

†Claims based on traditional homeopathic practice, not accepted medical evidence. Not FDA evaluated.

WARNINGS:

Professional Use Only

If pregnant or breast-feeding, ask a health professional before use.

In case of overdose, get medical help or contact a Poison Control Center right away.

If condition worsens, seek medical attention.

KEEP OUT OF REACH OF CHILDREN

Do not use if tamper evident seal is broken or missing.

Store in a cool place after opening

KEEP OUT OF REACH OF CHILDREN:

In case of overdose, get medical help or contact a Poison Control Center right away.

DIRECTIONS:

Adults 1 to 2 teaspoons one to two times daily. Children under twelve one half adult dosage. Consult a physician for use in children under 12 years of age.

INDICATIONS:

Provides potentized homeo-nutritional support and drainage in kidney and bladder disorders.†

†Claims based on traditional homeopathic practice, not accepted medical evidence. Not FDA evaluated.

INACTIVE INGREDIENTS:

Alcohol USP 20%, Purified Water USP.

QUESTIONS:

MANUFACTURED EXCLUSIVELY FOR

NUTRITIONAL SPECIALTIES, INC.

PO BOX 97227

PITTSBURG, PA 15229

www.phpltd.com

PACKAGE LABEL DISPLAY:

Professional

Health Products

HOMEOPATHIC

NDC 83027-0015-1

KIDNEY

LIQUESCENCE

4 FL. OZ (120 ml)